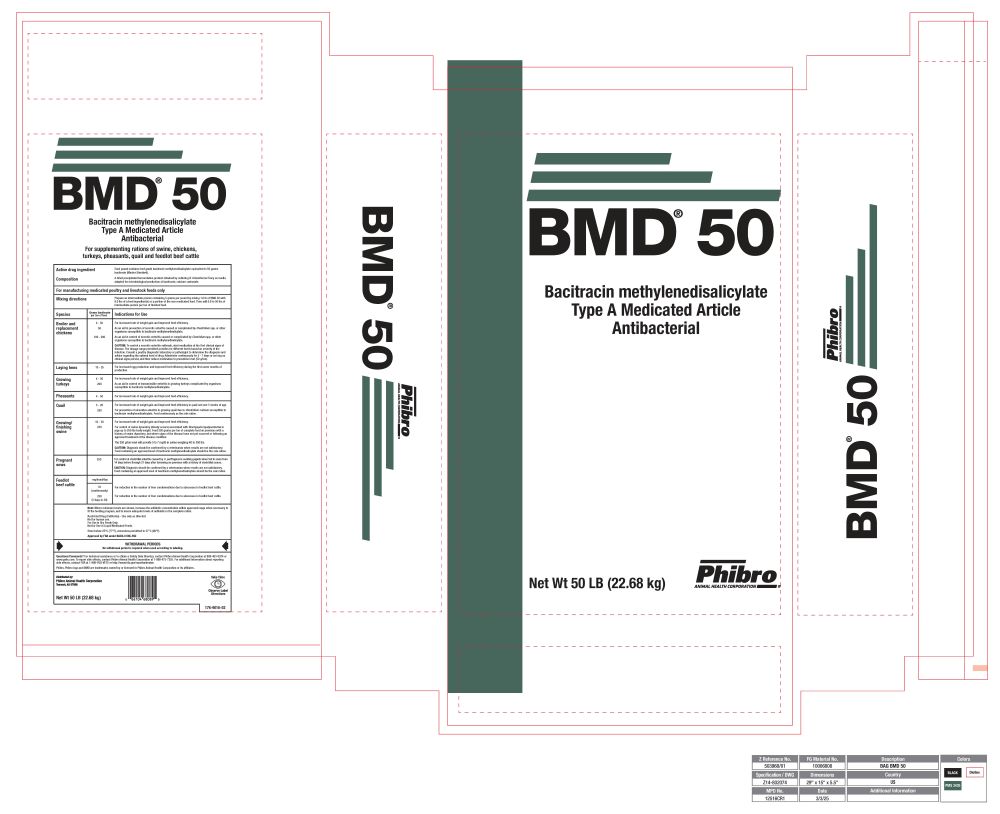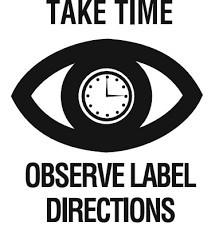 DRUG LABEL: BMD
NDC: 66104-1551 | Form: GRANULE
Manufacturer: Phibro Animal Health
Category: animal | Type: OTC TYPE A MEDICATED ARTICLE ANIMAL DRUG LABEL
Date: 20260224

ACTIVE INGREDIENTS: BACITRACIN METHYLENEDISALICYLATE 50 g/0.45 kg
INACTIVE INGREDIENTS: CALCIUM CARBONATE

BMD®
50

BMD® 50

Bacitracin methylenedisalicylate
Type A Medicated Article
Antibacterial

For supplementing rations of swine, chickens, turkeys, pheasants, quail and feedlot beef cattle

Active drug ingredient

Each pound contains feed grade bacitracin methylenedisalicylate equivalent to 50 grams bacitracin (Master Standard).

Composition

A dried precipitated fermentation product obtained by culturing B. licheniformis Tracy on media adapted for microbiological production of bacitracin; calcium carbonate.

PURPOSE

For manufacturing medicated poultry and livestock feeds only

Mixing directions

Prepare an intermediate premix containing 5 grams per pound by mixing 1.0 lb of BMD 50 with 9.0 lbs of a feed ingredient(s) or a portion of the non-medicated feed. Then add 0.8 to 50 lbs of intermediate premix per ton of finished feed.

VETERINARY INDICATIONS

Species | Grams bacitracin per ton of feed | Indications for use
Broiler and replacement chickens | 4 - 50 | For increased rate of weight gain and improved feed efficiency.
Broiler and replacement chickens
Broiler and replacement chickens | 50 | As an aid in prevention of necrotic enteritis caused or complicated by Clostridium spp. or other organisms susceptible to bacitracin methylenedisalicylate.
Broiler and replacement chickens
Broiler and replacement chickens | 100 - 200 | As an aid in control of necrotic enteritis caused or complicated by Clostridium spp. or other organisms susceptible to bacitracin methylenedisalicylate.
Broiler and replacement chickens
Broiler and replacement chickens |  | CAUTION: To control a necrotic enteritis outbreak, start medication at the first clinical signs of disease. The dosage range permitted provides for different levels based on severity of the infection. Consult a poultry diagnostic laboratory or pathologist to determine the diagnosis and advice regarding the optimal level of drug. Administer continuously for 5 - 7 days or as long as clinical signs persist, and then reduce medication to prevention level (50 g/ton).
Laying hens | 10 - 25 | For increased egg production and improved feed efficiency during the first seven months of production.
Growing turkeys | 4 - 50 | For increased rate of weight gain and improved feed efficiency.
Growing turkeys
Growing turkeys | 200 | As an aid in control of transmissible enteritis in growing turkeys complicated by organisms susceptible to bacitracin methylenedisalicylate.
Pheasants | 4 - 50 | For increased rate of weight gain and improved feed efficiency.
Quail | 5 - 20 | For increased rate of weight gain and improved feed efficiency in quail not over 5 weeks of age.
Quail
Quail | 200 | For prevention of ulcerative enteritis in growing quail due to Clostridium colinum susceptible to bacitracin methylenedisalicylate. Feed continuously as the sole ration.
Growing/finishing swine | 10 - 30 | For increased rate of weight gain and improved feed efficiency.
Growing/finishing swine
Growing/finishing swine | 250 | For control of swine dysentery (bloody scours) associated with Brachyspira hyodysenteriae in pigs up to 250 lbs body weight. Feed 250 grams per ton of complete feed on premises with a history of swine dysentery, but where signs of the disease have not yet occurred or following an approved treatment of the disease condition.
Growing/finishing swine
Growing/finishing swine |  | The 250 g/ton level will provide 5 to 7 mg/lb in swine weighing 40 to 250 lbs.
Growing/finishing swine
Growing/finishing swine |  | CAUTION: Diagnosis should be confirmed by a veterinarian when results are not satisfactory. Feed containing an approved level of bacitracin methylenedisalicylate should be the sole ration.
Pregnant sows | 250 | For control of clostridial enteritis caused by C. perfringens in suckling piglets when fed to sows from 14 days before through 21 days after farrowing on premises with a history of clostridial scours.
Pregnant sows
Pregnant sows |  | CAUTION: Diagnosis should be confirmed by a veterinarian when results are not satisfactory. Feed containing an approved level of bacitracin methylenedisalicylate should be the sole ration.
Feedlot beef cattle | mg/head/day
Feedlot beef cattle | 70 (continuously) | For reduction in the number of liver condemnations due to abscesses in feedlot beef cattle.
Feedlot beef cattle
Feedlot beef cattle | 250 (5 days in 30) | For reduction in the number of liver condemnations due to abscesses in feedlot beef cattle.

Note: Where minimum levels are shown, increase the antibiotic concentration within approved range when necessary to fit the feeding program, and to insure adequate levels of antibiotic in the complete ration.
Restricted Drug (California) - Use only as directed.
Not for human use.
For Use in Dry Feeds Only.
Not for Use in Liquid Medicated Feeds.
Store below 25°C (77°F), excursions permitted to 37°C (99°F).
Approved by FDA under NADA # 046-592

WITHDRAWAL PERIODS

No withdrawal period is required when used according to labeling.

Questions/Comments? For technical assistance or to obtain a Safety Data Sheet(s), contact Phibro Animal
Health at 888-403-0074 or www.pahc.com. To report side effects, contact Phibro Animal Health Corporation at
1-888-475-7355. For additional information about reporting side effects for animal drugs, contact FDA at
1-888-FDA-VETS or http://www.fda.gov/reportanimalae

Phibro, Phibro logo and BMD are trademarks owned by or licensed to Phibro Animal Health Corporation or its affiliates.

Distributed by:
Phibro Animal Health Corporation
Teaneck, NJ 07666

Net Wt 50 LB (22.68 kg)
176-9016-02

BMD 50

BMD 50 Label